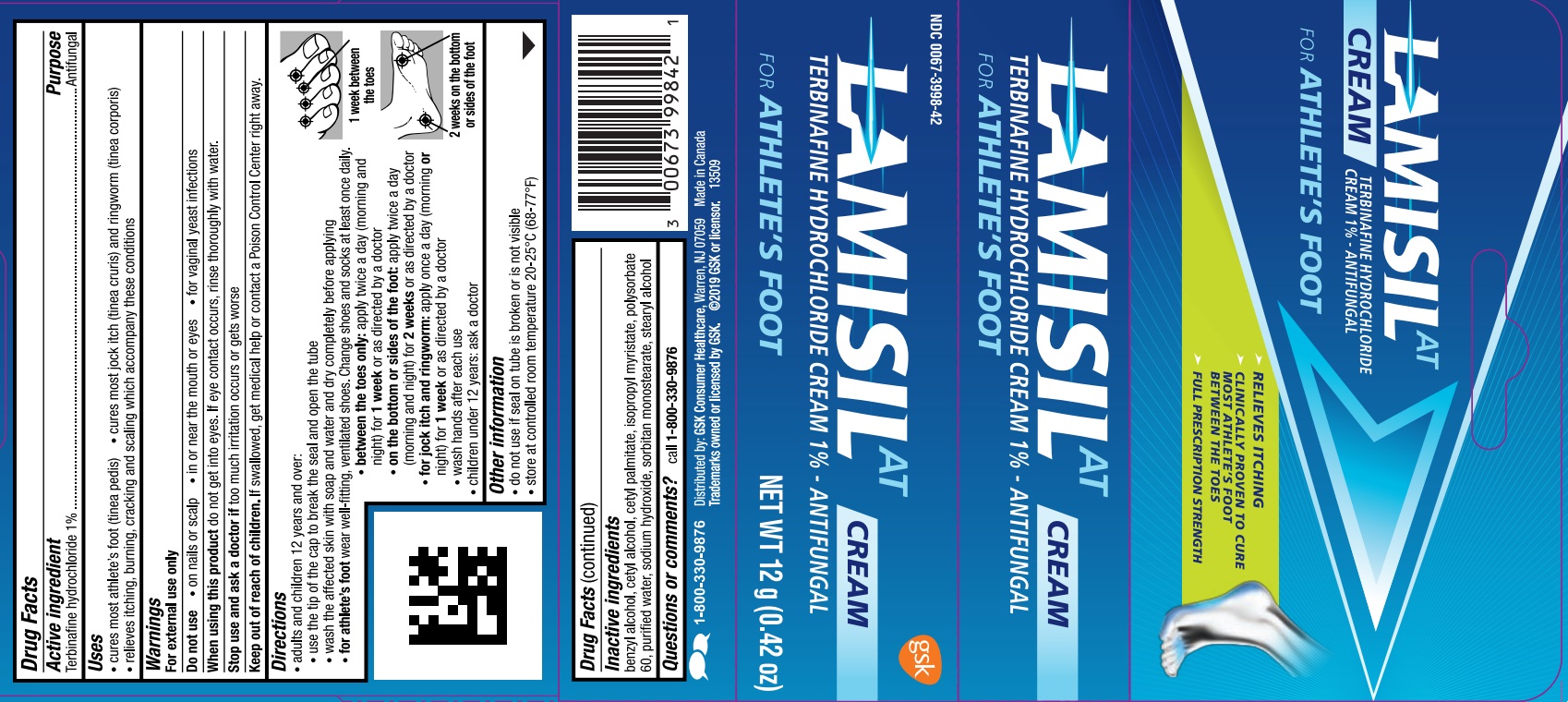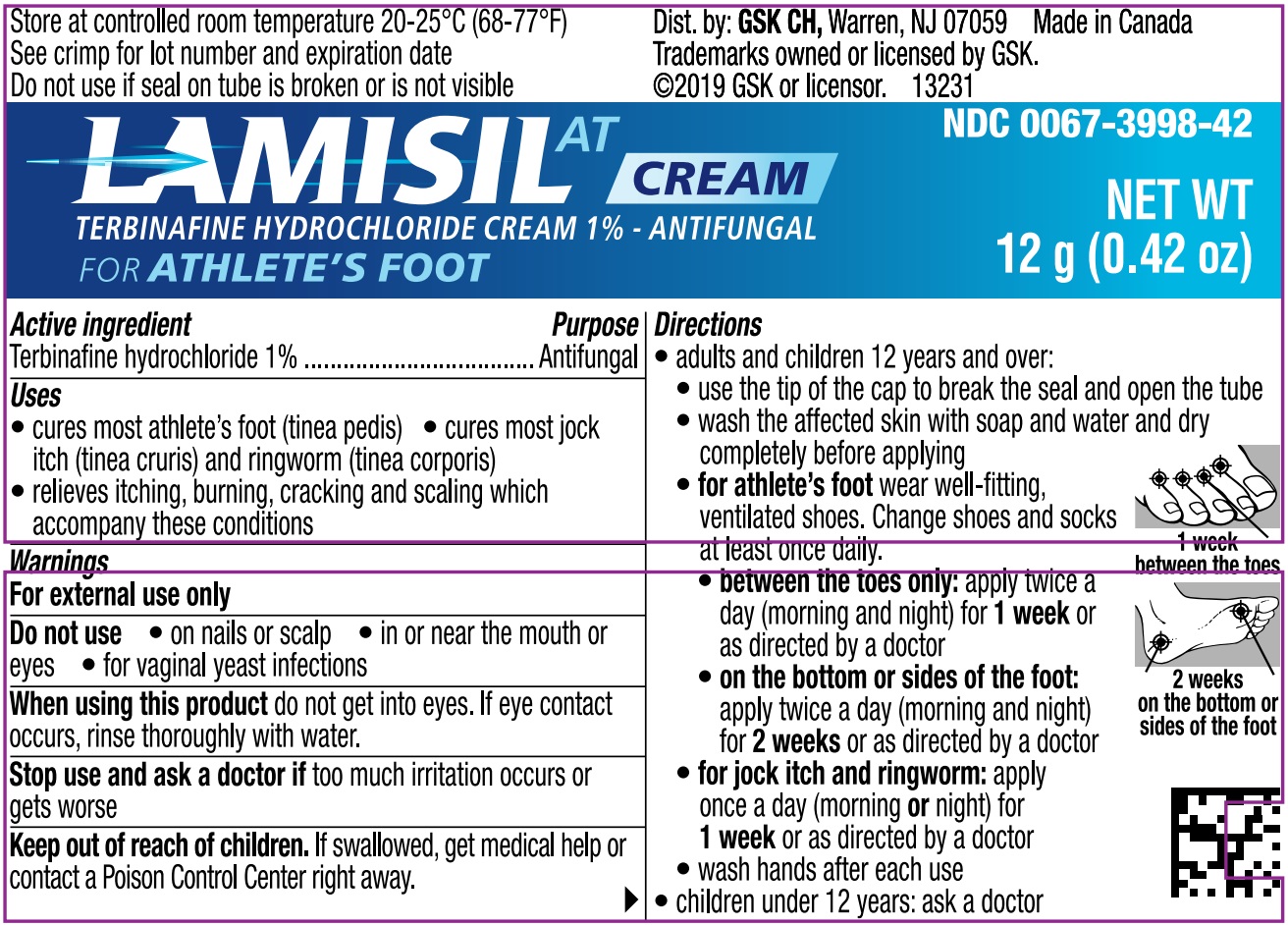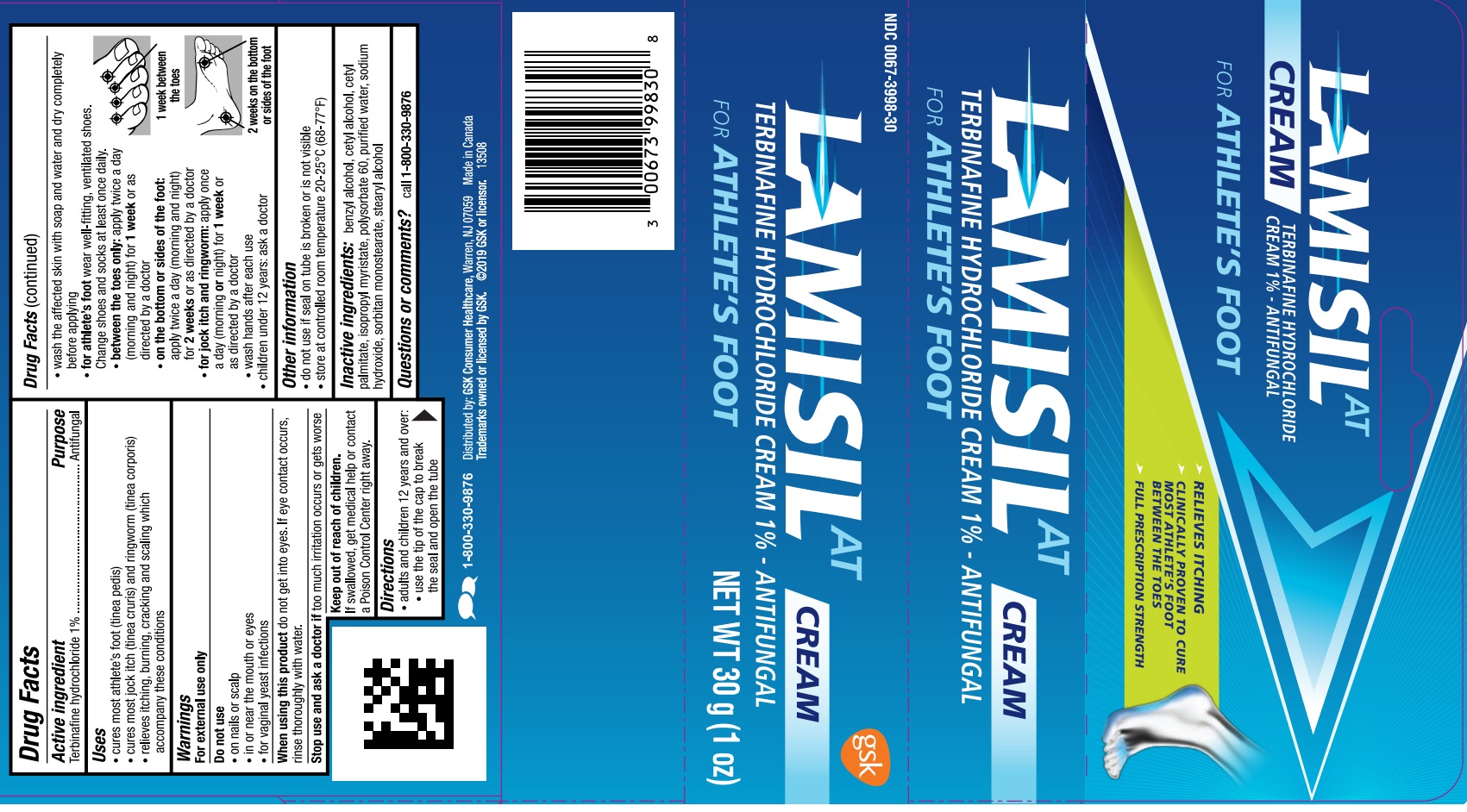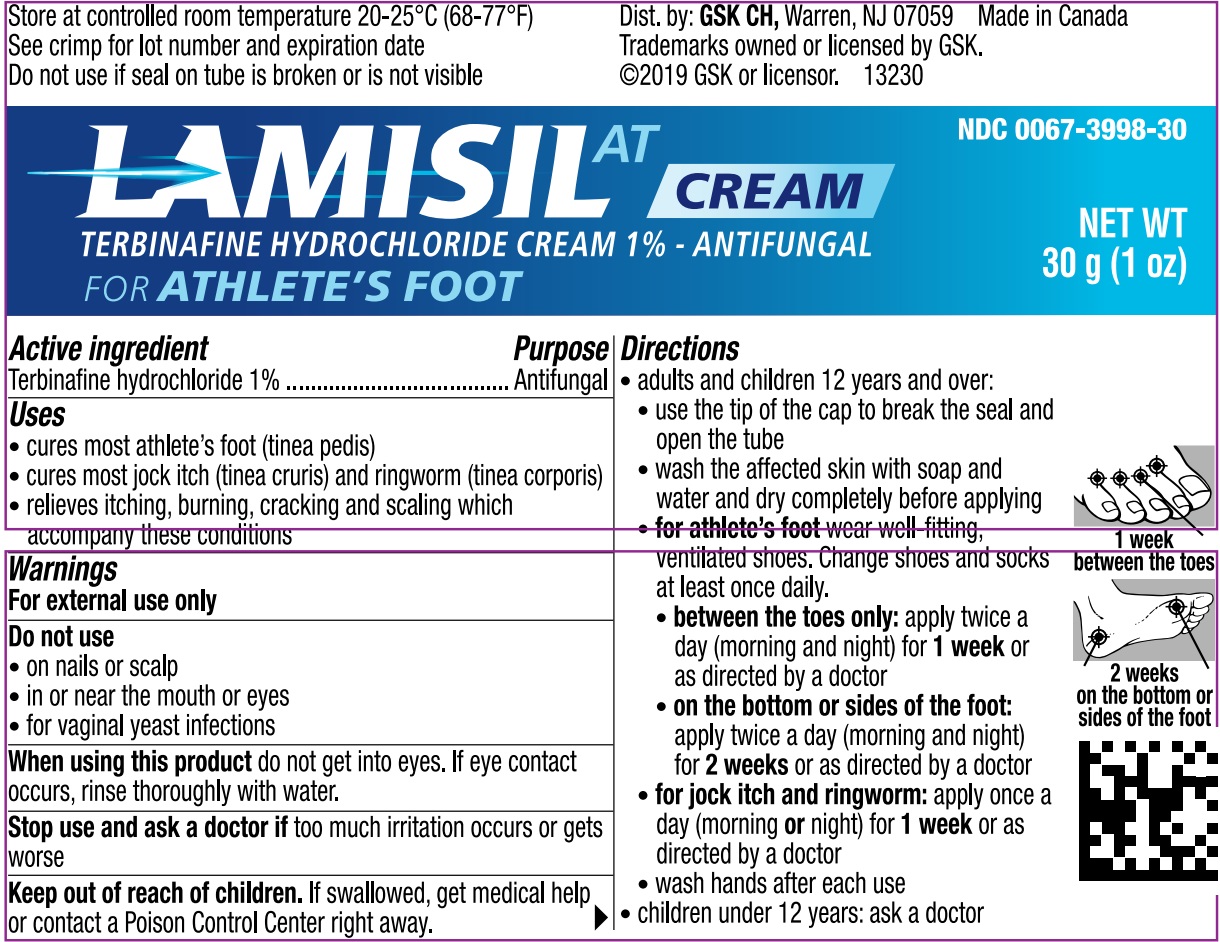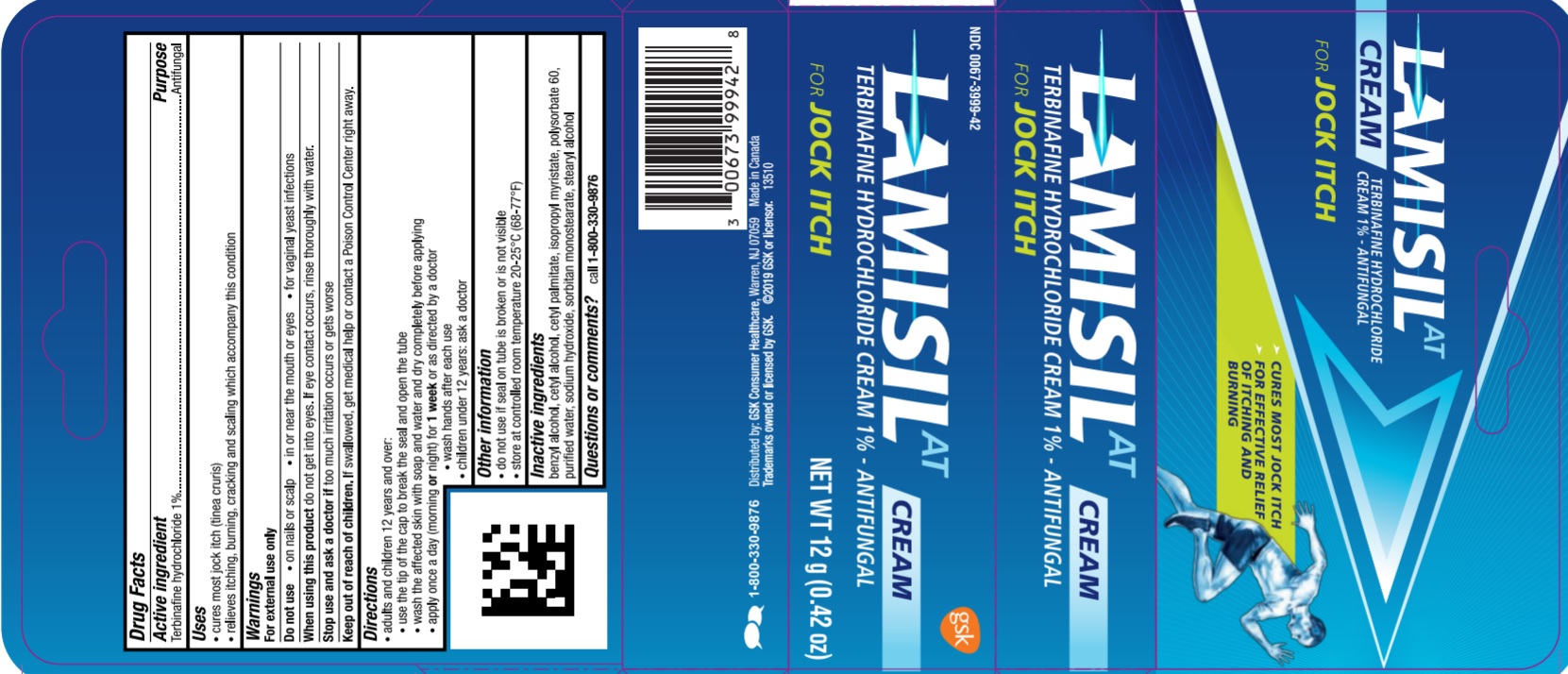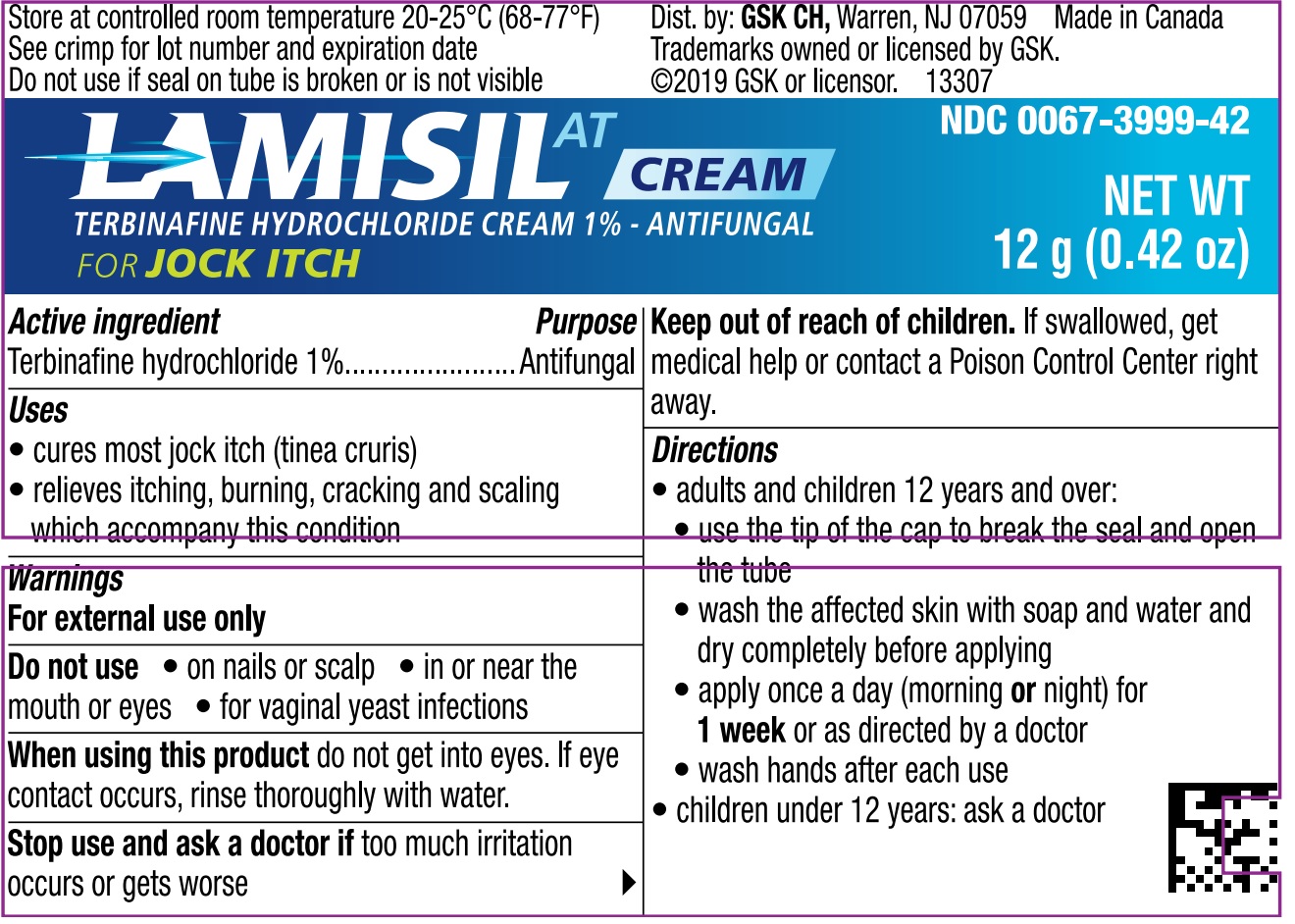 DRUG LABEL: Lamisil AT Cream
NDC: 61047-120 | Form: CREAM
Manufacturer: Voyant Beauty Inc.
Category: otc | Type: HUMAN OTC DRUG LABEL
Date: 20251118

ACTIVE INGREDIENTS: TERBINAFINE HYDROCHLORIDE 1 g/100 g
INACTIVE INGREDIENTS: CETYL PALMITATE; ISOPROPYL MYRISTATE; WATER; SODIUM HYDROXIDE; SORBITAN MONOSTEARATE; CETYL ALCOHOL; POLYSORBATE 60; STEARYL ALCOHOL; BENZYL ALCOHOL

Formula# 39900

ACTIVE INGREDIENT

Terbinafine hydrochloride 1%

PURPOSE

Antifungal

Uses

- cure most jock itch (tinea cruris) and ringworm (tinea corporis)

- relieves itching, burning, cracking andf scaling which accompany this condition

Warnings

For external use only

Do not use

- on nails or scalp

- in or near the mouth or eyes

- for vaginal yeast infections

When using this product do not get into eyes. If eye contact occurs, rinse thoroughly with water

Stop use and ask a doctor if too much irritation occurs or gets worse

Keep out of reach of children. If swallowed, get medical help or contact a Poison Control Center right away.

Directions

- adults and children 12 years and over:

- use the tip of the cap to break the seal and open the tube
- wash the affected skin with soap and water and dry completely before applying
- for athlete's foot wear well-fitting, ventilated shoes. Change shoes and socks at least once daily.
- between the toes only: apply twice a day (morning and night) for 1 week or as directed by a doctor
- on the bottom or sides of the foot: apply twice a day (morning and night) for 2 weeks or as directed by a doctor
- for jock itch and ringworm: apply once a day (morning or night) for 1 week or as directed by a doctor
- wash hands after each use

- children under 12 years: ask a doctor

Other Information

- do no use if seal on tube is broken or is not visible

- store at controlled room temperature 20-25C (68-77F)

Inactive Ingredients

benzyl alcohol, cetyl alcohol, cetyl palmitate, isopropyl myristate, polysorbate 60, purified water, sodium hydroxide, sorbitan monostearate, stearly alcohol

Questions or comments?

call 1-800-330-9876

12 g Tube with Carton - For Jock Itch

Lamisil AT

Cream Terbinafine Hydrochloride Cream 1% - Antifungal

For JOCK ITCH

- cures most jock itch

- for effective relief of itching and burning

NET WT

12 g (0.42 oz)

12 g Tube with Carton - For Athlete's Foot

Lamisil AT Cream

Terbinafine Hydrochloride Cream 1% - Antifungal

For Athlete's Foot

Net Wt

12 g (0.42 oz)

30 g Tube with Carton - For Athlete's Foot

Lamisil AT Cream

Terbinafine Hydrochloride Cream 1% - Antifungal

For Athlete's Foot

NET WT

30 g (1 oz)